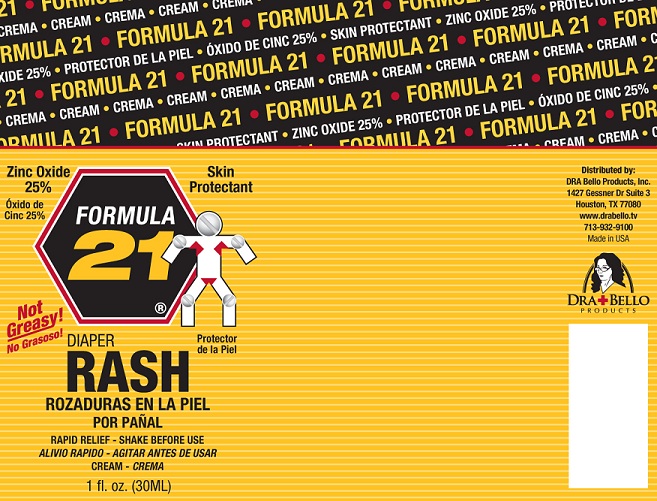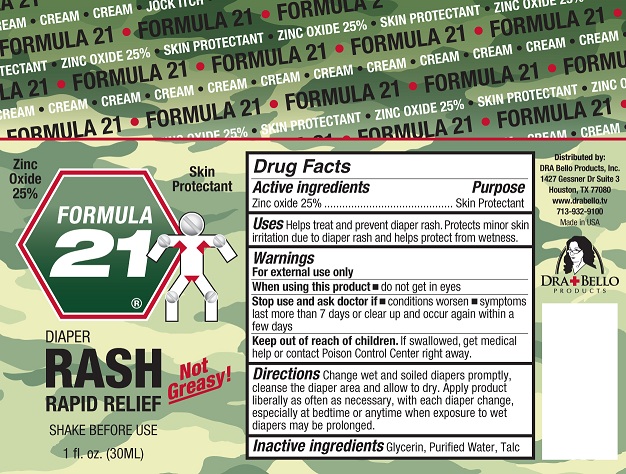 DRUG LABEL: Formula 21 Diaper Rash
NDC: 42416-0021 | Form: CREAM
Manufacturer: DRA Bello Products, Inc.
Category: otc | Type: HUMAN OTC DRUG LABEL
Date: 20120124

ACTIVE INGREDIENTS: ZINC OXIDE 25 mL/100 mL
INACTIVE INGREDIENTS: GLYCERIN; WATER; TALC

Formula 21 Diaper Rash Cream

Active Ingredient

Zinc Oxide 25%

Purpose

Skin Protectant

Uses

Helps treat and prevent diaper rash. Protects minor skin irritation due to diaper rash and helps protect from wetness.

Warnings

For external use only.

When using this product

Do not get in eyes.

Stop use and as doctor if

- conditions worsen
- symptoms last more than 7 days or clear up and return again within a few days

Keep out of reach of children.

If swallowed, get medical help or contact Poison Control Center right away.

Directions

Change wet and soiled diapers promptly, cleanse the diaper area and allow to dry. Apply product liberally as often as necessary, with each diaper change especially at bedtime or any time when exposure to wet diapers may be prolonged.

Inactive Ingredients

Glycerin, Purified Water, Talc

Product Label

Formula 21
Zinc Oxide 25%

Skin Protectant

Not Greasy!

Protector

Diaper Rash - Rapid Relief- Shake before use - Cream

1 fl. oz. (30ml)

Distributed by DRA Bello Products, Inc.
1627 Gessner Dr. Suite 3
Houston TX 77080

www.drabello.tv

713-932-9100